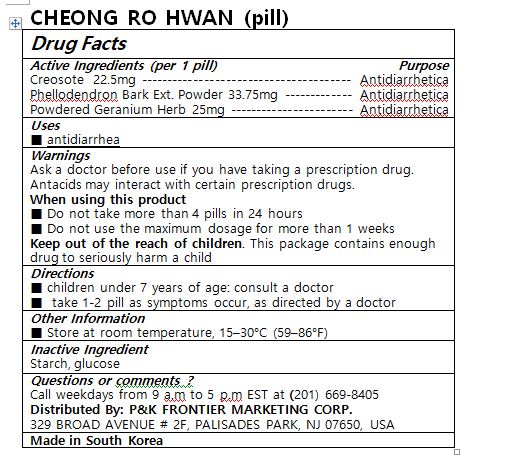 DRUG LABEL: CHEONG RO HWAN
NDC: 72689-0029 | Form: PILL
Manufacturer: OASIS TRADING
Category: otc | Type: HUMAN OTC DRUG LABEL
Date: 20181213

ACTIVE INGREDIENTS: WOOD CREOSOTE 44.4 mg/1 1
INACTIVE INGREDIENTS: SOYBEAN OIL; STARCH, RICE

ACTIVE INGREDIENT

creosote, phellodendron bark ext. powder, powdered geranium herb

PURPOSE

■ antidiarrhea

Keep out of reach of children

INDICATIONS AND USAGE

■ children under 7 years of age: consult a doctor

■ take 1-2 tablet as symptoms accur, as directed by a doctor

Ask a doctor before use if you have taking a prescription drug. Antacids may interact with certain prescription drugs.

When using this product

■ Do not take more than 4 pills in 24 hours

■ Do not use the maximum dosage for more than 1 weeks

Keep out of the reach of children. This package contains enough drug to seriously harm a child

INACTIVE INGREDIENT

starch, glucose

DOSAGE AND ADMINISTRATION

For oral use only